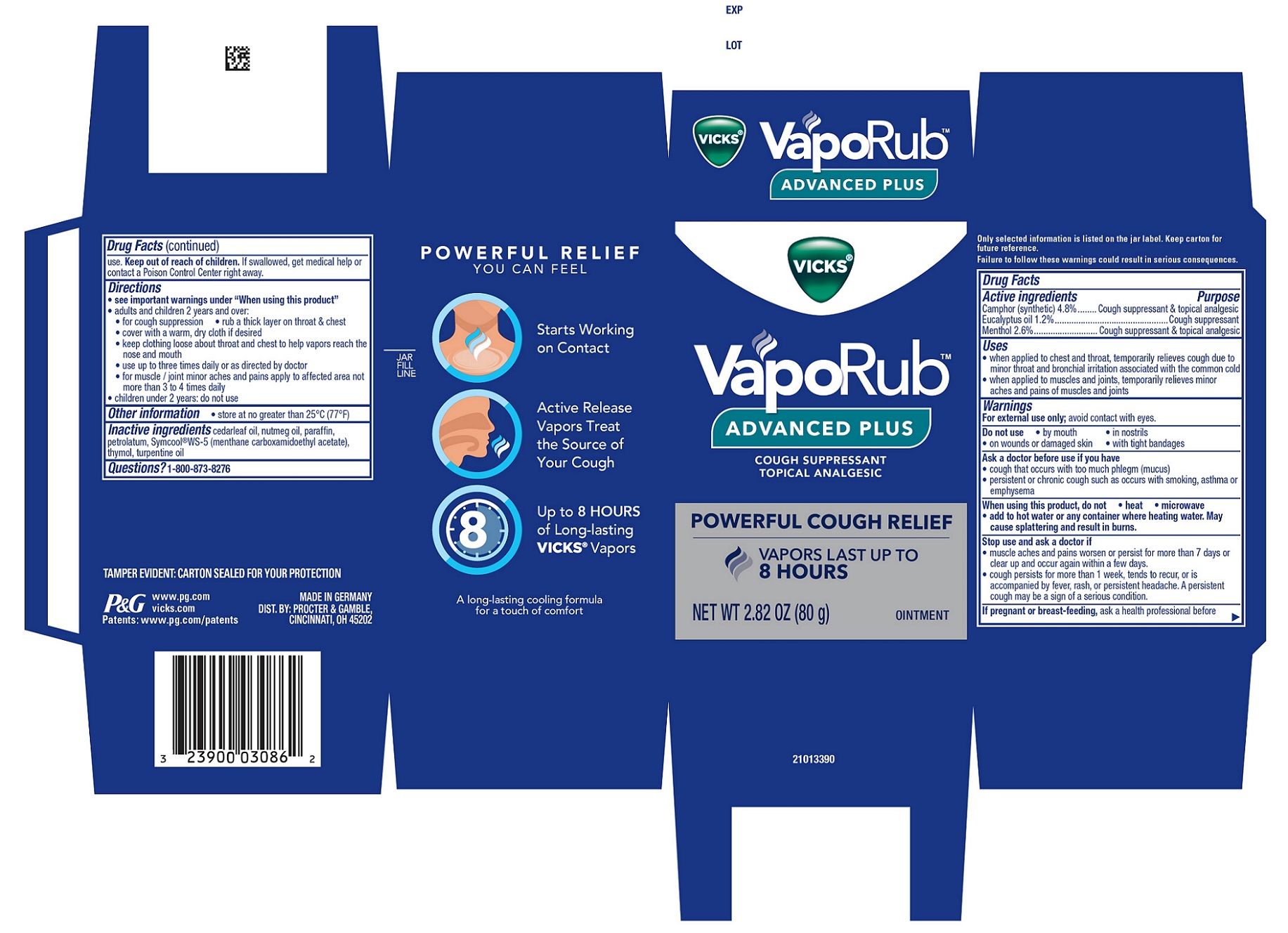 DRUG LABEL: Vicks VapoRub ADVANCED PLUS
NDC: 64336-001 | Form: OINTMENT
Manufacturer: Procter & Gamble Manufacturing GmbH
Category: otc | Type: HUMAN OTC DRUG LABEL
Date: 20251001

ACTIVE INGREDIENTS: EUCALYPTUS OIL 0.012 g/1 g; MENTHOL, UNSPECIFIED FORM 0.026 g/1 g; CAMPHOR (SYNTHETIC) 0.048 g/1 g
INACTIVE INGREDIENTS: N-((ETHOXYCARBONYL)METHYL)-P-MENTHANE-3-CARBOXAMIDE; PARAFFIN; TURPENTINE OIL; PETROLATUM; THYMOL; CEDAR LEAF OIL; NUTMEG OIL

Vicks® VapoRub™ ADVANCED PLUS

Drug Facts

Active ingredients

Camphor (synthetic) 4.8%
Eucalyptus oil 1.2%
Menthol 2.6%

Active ingredients Purpose

Cough suppressant & topical analgesic
Cough suppressant
Cough suppressant & topical analgesic

Uses

• when applied to chest and throat, temporarily relieves cough due to minor throat and bronchial irritation associated with the common cold
• when applied to muscles and joints, temporarily relieves minor aches and pains of muscles and joints

Warnings

For external use only; avoid contact with eyes.

Do not use

• by mouth

• in nostrils

• on wounds or damaged skin

• with tight bandages

Ask a doctor before use if you have

• cough that occurs with too much phlegm (mucus)

• persistent or chronic cough such as occurs with smoking, asthma or emphysema

When using this product

do not

• heat

• microwave

• add to hot water or any container where heating water. May cause splattering and result in burns.

Stop use and ask a doctor if

• muscle aches and pains worsen or persist for more than 7 days or clear up and occur again within a few days.

• cough persists for more than 1 week, tends to recur, or is accompanied by fever, rash, or persistent headache. A persistent cough may be a sign of a serious condition.

If pregnant or breast-feeding,

ask a health professional before use.

Keep out of reach of children.

OVERDOSAGE

If swallowed, get medical help or contact a Poison Control Center right away.

Directions

• see important warnings under “When using this product”

• adults and children 2 years and over:

• for cough suppression • rub a thick layer on throat & chest

• cover with a warm, dry cloth if desired

• keep clothing loose about throat and chest to help vapors reach the nose and mouth

• use up to three times daily or as directed by doctor

• for muscle / joint minor aches and pains apply to affected area not more than 3 to 4 times daily

• children under 2 years: do not use

Other information

• store at no greater than 25°C (77°F)

Inactive ingredients

cedarleaf oil, nutmeg oil, paraffin, petrolatum, Symcool®WS-5 (menthane carboxamidoethyl acetate), thymol, turpentine oil

Questions?

1-800-873-8276

TAMPER EVIDENT: CARTON SEALED FOR YOUR PROTECTION

MADE IN GERMANY
DIST. BY: PROCTER & GAMBLE,
CINCINNATI, OH 45202

PRINCIPAL DISPLAY PANEL - 2.82 OZ (80 g) jar

NEW

VICKS®

VapoRub™

ADVANCED PLUS

COUGH SUPPRESSANT

TOPICAL ANALGESIC

POWERFUL COUGH RELIEF

VAPORS LAST UP TO 8 HOURS

NET WT 2.82 OZ (80 g)

OINTMENT